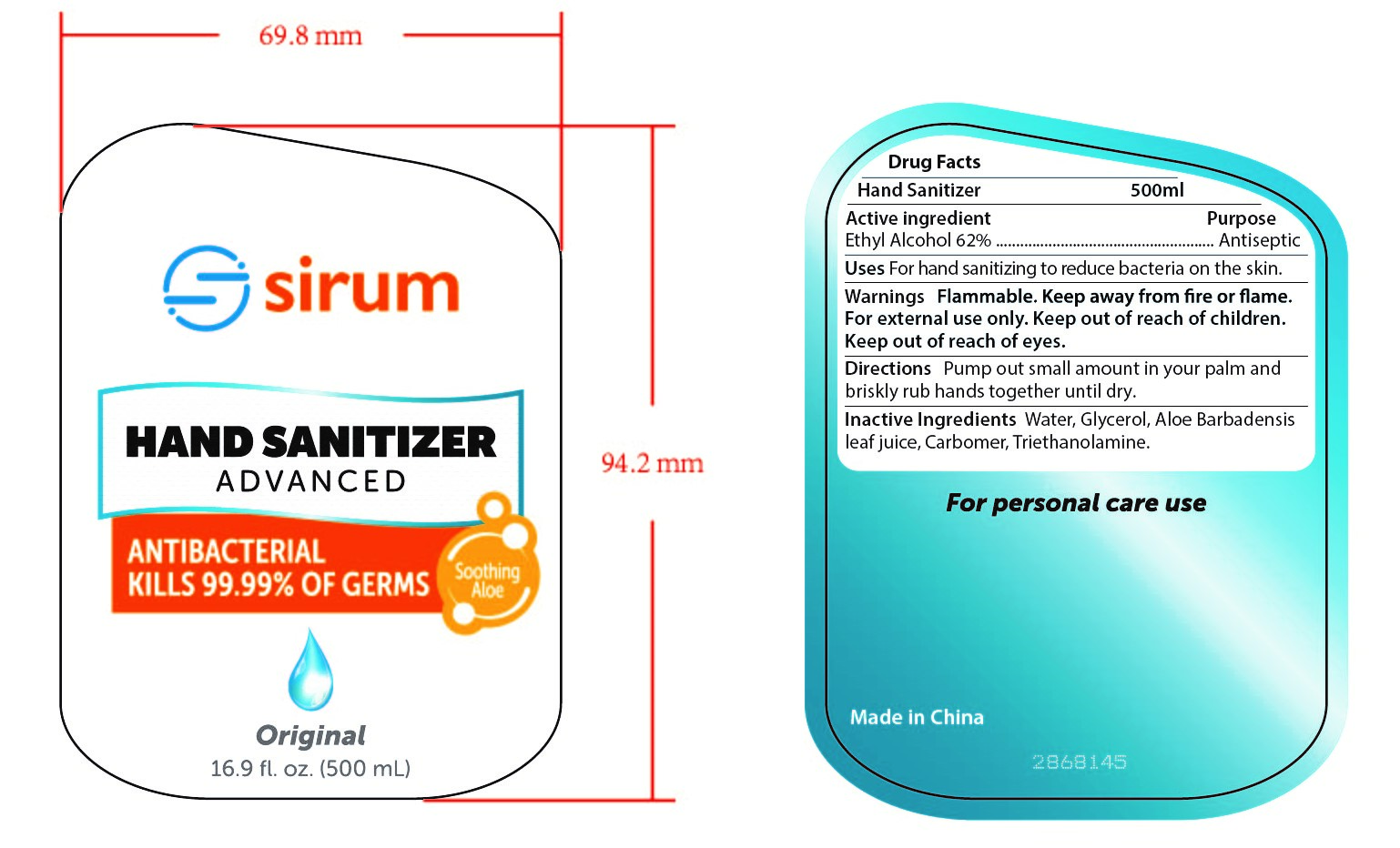 DRUG LABEL: HAND SANITIZER
NDC: 47993-251 | Form: GEL
Manufacturer: NINGBO JIANGBEI OCEAN STAR TRADING CO.,LTD
Category: otc | Type: HUMAN OTC DRUG LABEL
Date: 20201104

ACTIVE INGREDIENTS: ALCOHOL 62 g/112 mL
INACTIVE INGREDIENTS: TRIETHANOLAMINE BENZOATE; CARBOMER 940 0.3 g/112 mL; WATER; GLYCERIN 2 g/112 mL; ALOE VERA LEAF

47993-251

Active ingredients

Ethyl Alcohol 62%

PURPOSE

Antiseptic

Warnings:

Flammable. Keep away from fire or flame. For external use only. Keep out of reach of children. Keep out of reach of eyes.

Uses：

For hand sanitizing to readuce bacteria on the skin.

Directions:

Pump out small amount in your palm and briskly rub hands together until dry.

Keep out of reach of children.

Inactive Ingredients:

Water,Glycerin,Aloe Barbadensis Leaf Juice,Carbomer,Triethanolamine